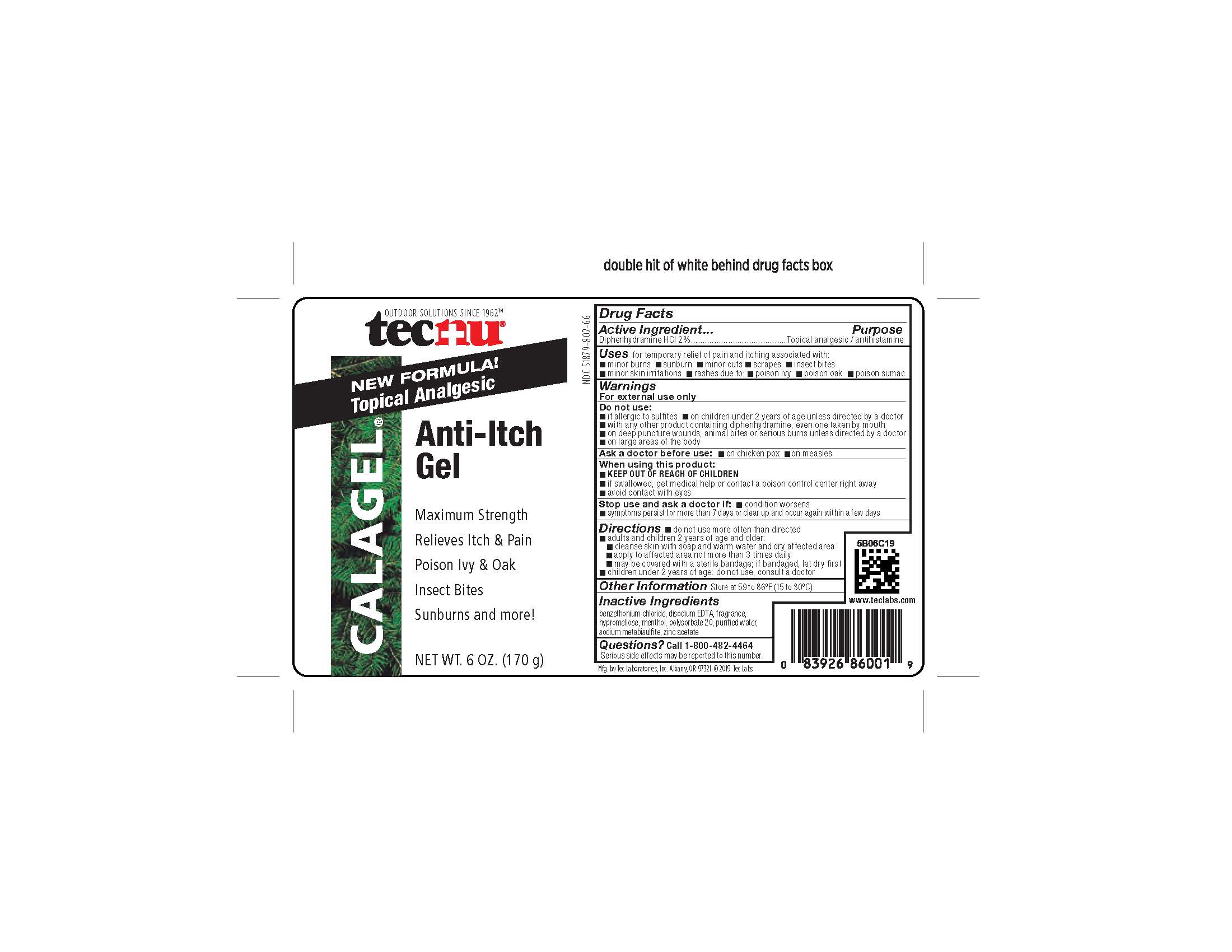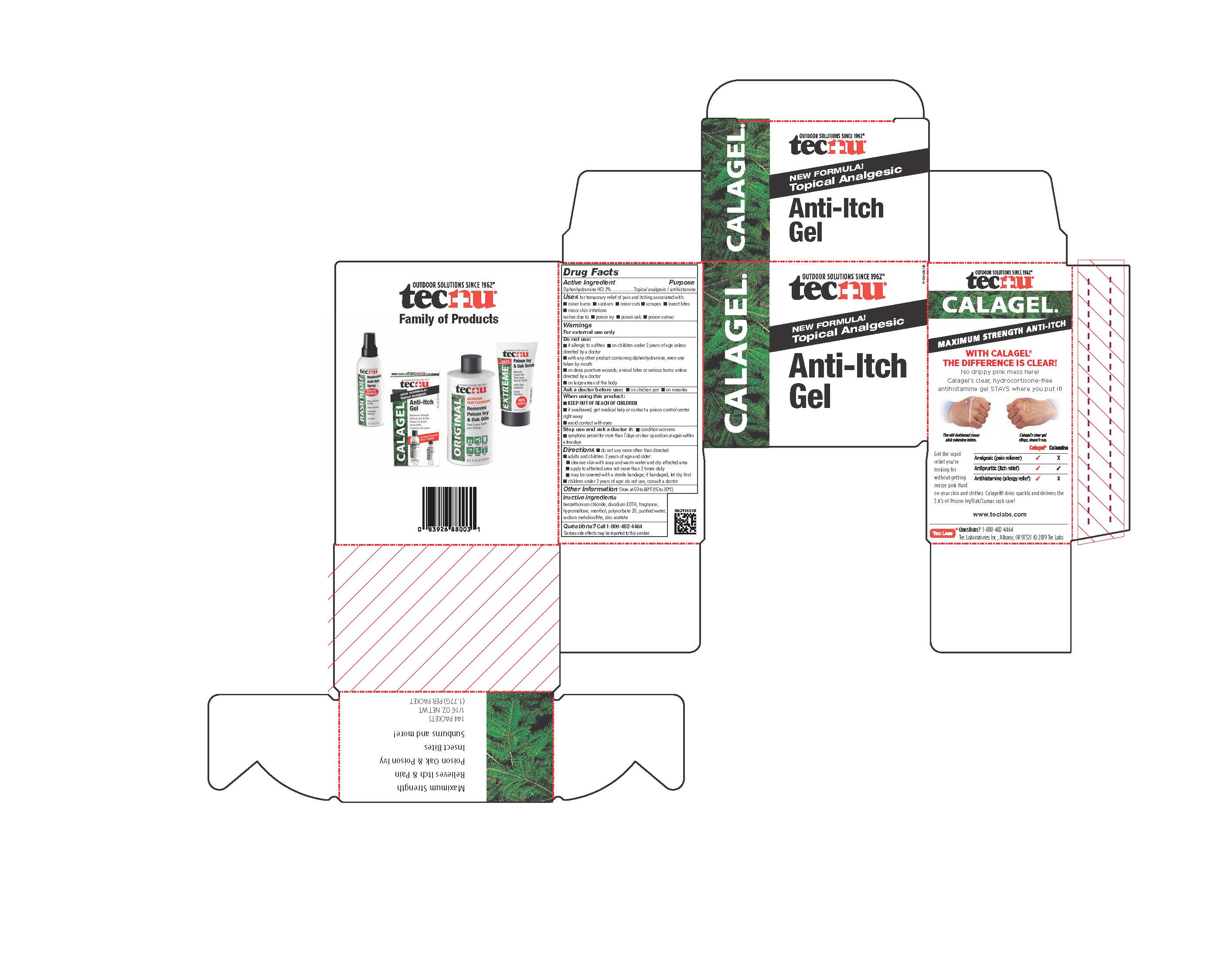 DRUG LABEL: Tecnu Calagel
NDC: 51879-802 | Form: GEL
Manufacturer: Tec Laboratories Inc.
Category: otc | Type: HUMAN OTC DRUG LABEL
Date: 20251017

ACTIVE INGREDIENTS: DIPHENHYDRAMINE HYDROCHLORIDE 20 mg/1 g
INACTIVE INGREDIENTS: POLYSORBATE 20; ZINC ACETATE; HYPROMELLOSE 2208 (100 MPA.S); WATER; MENTHOL, UNSPECIFIED FORM; BENZETHONIUM CHLORIDE; SODIUM METABISULFITE; EDETATE DISODIUM

Tecnu Calagel

ACTIVE INGREDIENT

Diphenhydramine HCL 2%

Purpose Topical analgesic / antihistamine

INDICATIONS AND USAGE

for temporary relief of pain and itching associated with:

•minor burns •sunburn •minor cuts •scrapes •insect bites

•minor skin irritations

rashes due to: •poison oak •poison ivy •poison sumac

DO NOT USE:

•if allergic to sulfites •on children under 2 years of age unless directed by a doctor

•with any other products containing diphenydramine, even one taken by mouth

•on deep puncture wounds, animal bites or serious burns unless directed by a doctor

•on large areas of the body

ASK DOCTOR

•on chicken pox •on measles

When using this product:

•KEEP OUT OF REACH OF CHILDREN

•if swallowed, get medical help or contact a poison control center right away

•avoid contact with eyes

Stop use and ask a doctor if: •condition worsens

•symptoms persist for more than 7 days or clear up and occur again within a few days

DOSAGE AND ADMINISTRATION

Directions •do not use more often than directed

•adults and children 2 years of age and older

•cleanse skin with soap and warm water and dry affected area

•apply to affected area not more than 3 times daily

•may be covered with a sterile bandage, if bandaged, let dry first

•children under 2 years of age do not use, consult a doctor

Other Information Store at 59 to 86ºF (15 to 30ºC)

INACTIVE INGREDIENT

benzethonium chloride, disodium EDTA, fragrance, hypromellose,

menthol, polysorbate 20, purified water, sodium metabisulfite, zinc acetate

Questions? Call 1-800-482-4464

serious side effects may be reported to this number.